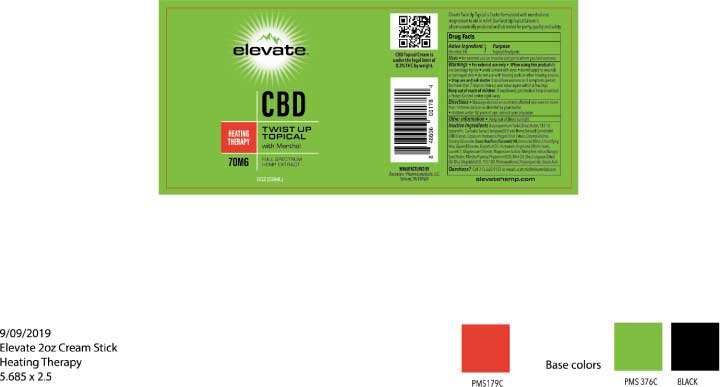 DRUG LABEL: Elevate Heating Therapy TWIST UP
NDC: 76348-454 | Form: CREAM
Manufacturer: RENU LABORATORIES, INC.
Category: otc | Type: HUMAN OTC DRUG LABEL
Date: 20220113

ACTIVE INGREDIENTS: MENTHOL 2.8 g/56 g
INACTIVE INGREDIENTS: CANNABIDIOL; CANNABIS SATIVA SEED OIL; CETEARYL GLUCOSIDE; MAGNESIUM CHLORIDE; STEARIC ACID; GLYCERYL MONOSTEARATE; LAURETH-7; WITCH HAZEL; POLYACRYLAMIDE (10000 MW); MANGIFERA INDICA SEED BUTTER; OLIVE OIL; CORN OIL; COCONUT OIL; C13-14 ISOPARAFFIN; PEG-100 STEARATE; PEPPERMINT OIL; CETOSTEARYL ALCOHOL; WATER; SHEA BUTTER; TABASCO PEPPER; WHITE WAX; PHENOXYETHANOL; MAGNESIUM SULFATE, UNSPECIFIED FORM

ELEVATE HEATING THERAPY TWIST UP

Active Ingredient

Menthol 5%

Purpose

Topical Analgesic

Uses

- For external use on muscles and joints where you feel soreness

Warnings

- For external use only
- When using this product do not bandage tightly
- avoid contact with eyes
- do not apply to wounds or damaged skin
- do not use with heating pads or other heating devices

- Stop use and ask doctor if condition worsens or if symptoms persist for more than 7 days or clear up and occur again within a few days.

Keep out of reach of children. If swallowed, get medical help or contact a Poison Control center right away.

Directions

- Massage desired amount into affected skin area no more than 10 times daily or as directed by your doctor.
- children under 12 years of age consult your physician.

Other information

- Keep out of direct sunlight.

INACTIVE INGREDIENT

Inactive Ingredients Butyrospermum Parkii (Shea) Butter, C13-14 Isoparaffin, Cannabis Sativa (Hempseed) Oil and Hemp Derived Cannabidiol (CBD) Extract, Capsicum Frutescens (Pepper) Fruit Extract, Cetearyl Alcohol, Cetearyl Glucoside, Cocos Nucifera (Coconut) Oil, Deionized Water, Emulsifying Wax, Glyceryl Stearate, Grapefruit Oil, Hamamelis Virginiana (Witch Hazel), Laureth-7, Magnesium Chloride, Magnesium Sulfate, Mangifera Indica (Mango) Seed Butter, Mentha Piperita (Peppermint) Oil, Mint Oil, Olea Europaea (Olive) Oil, Olus (Vegetable) Oil, PEG-100, Phenoxyethanol, Polyacrylamide, Stearic Acid

QUESTIONS

Questions? Call 215.660.9123 or email us at info@elevatecbd.com

DOSAGE AND ADMINISTRATION

Massage desired amount into affected skin area no more than 10 times daily or as directed by your doctor

RECENT MAJOR CHANGES

Dosage and Administration section did not exist prior to 01-06-2020. It was missed and created today.

Bullet mark only was removed.

Removed the word "Directions."

PACKAGE LABEL

Elevate 2oz Cream Stick